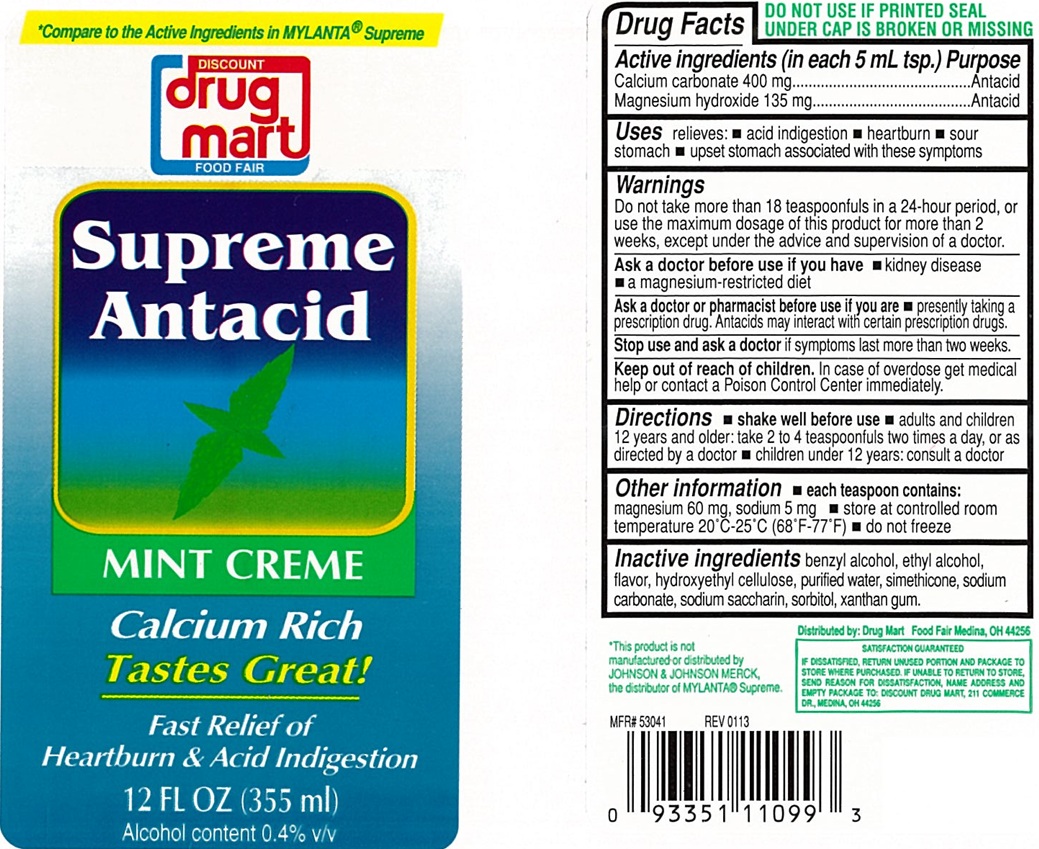 DRUG LABEL: Supreme Antacid
NDC: 53943-614 | Form: LIQUID
Manufacturer: Discount Drug Mart, Inc
Category: otc | Type: Human OTC Drug Label
Date: 20250227

ACTIVE INGREDIENTS: MAGNESIUM HYDROXIDE 135 mg/5 mL; CALCIUM CARBONATE 400 mg/5 mL
INACTIVE INGREDIENTS: BENZYL ALCOHOL; ALCOHOL; HYDROXYETHYL CELLULOSE (2000 MPA.S AT 1%); WATER; SACCHARIN SODIUM; SORBITOL; DIMETHICONE; SODIUM CARBONATE; XANTHAN GUM

Supreme Antacid Mint Creme

ACTIVE INGREDIENT (in each 5 mL)

Calcium carbonate 400 mg
Magnesium hydroxide 135 mg

PURPOSE

Antacid
Antacid

USE(S)

relieves:

- acid indigestion
- heartburn
- sour stomach
- upset stomach associated with these symptoms

WARNINGS

Do not take more than 18 teaspoonfuls in a 24-hour period, or use the maximum dosage of this product for more than 2 weeks, except under the advice and supervision of a doctor.

ASK A DOCTOR BEFORE USE IF YOU HAVE

- kidney disease
- a magnesium-restricted diet

ASK A DOCTOR OR PHARMACIST BEFORE USE IF YOU ARE

- presently taking a prescription drug. Antacids may interact with certain prescription drugs.

STOP USE AND ASK DOCTOR

if symptoms last more than two weeks

KEEP OUT OF REACH OF CHILDREN

In case of overdose get medical help or contact a Poison Control Center immediately.

DIRECTIONS

- shake well before use
- adults and children 12 years and older: take 2 to 4 teaspoonfuls two times a day, or as directed by a doctor
- children under 12 years: consult a doctor

OTHER INFORMATION

- each 10 mL contains: magnesium 60 mg, sodium 5 mg
- store at controlled room temperature 20ºC-25ºC (68º-77ºF)
- do not freeze

INACTIVE INGREDIENTS

benzyl alcohol, ethyl alcohol, flavor, hydroxyethyl cellulose, purified water, saccharin sodium, simethicone, sodium carbonate, sorbitol, xanthan gum.

PRINCIPAL DISPLAY PANEL

*Compare to the Active Ingredients in MYLANTA® Supreme
DISCOUNT drug mart

FOOD FAIR

Supreme
Antacid
MINT CREME
Calcium Rich

Taste Great!

Fast Relief of
Heartburn & Acid Indigestion
12 FL OZ (355 mL)
Alcohol content 0.4% v/v